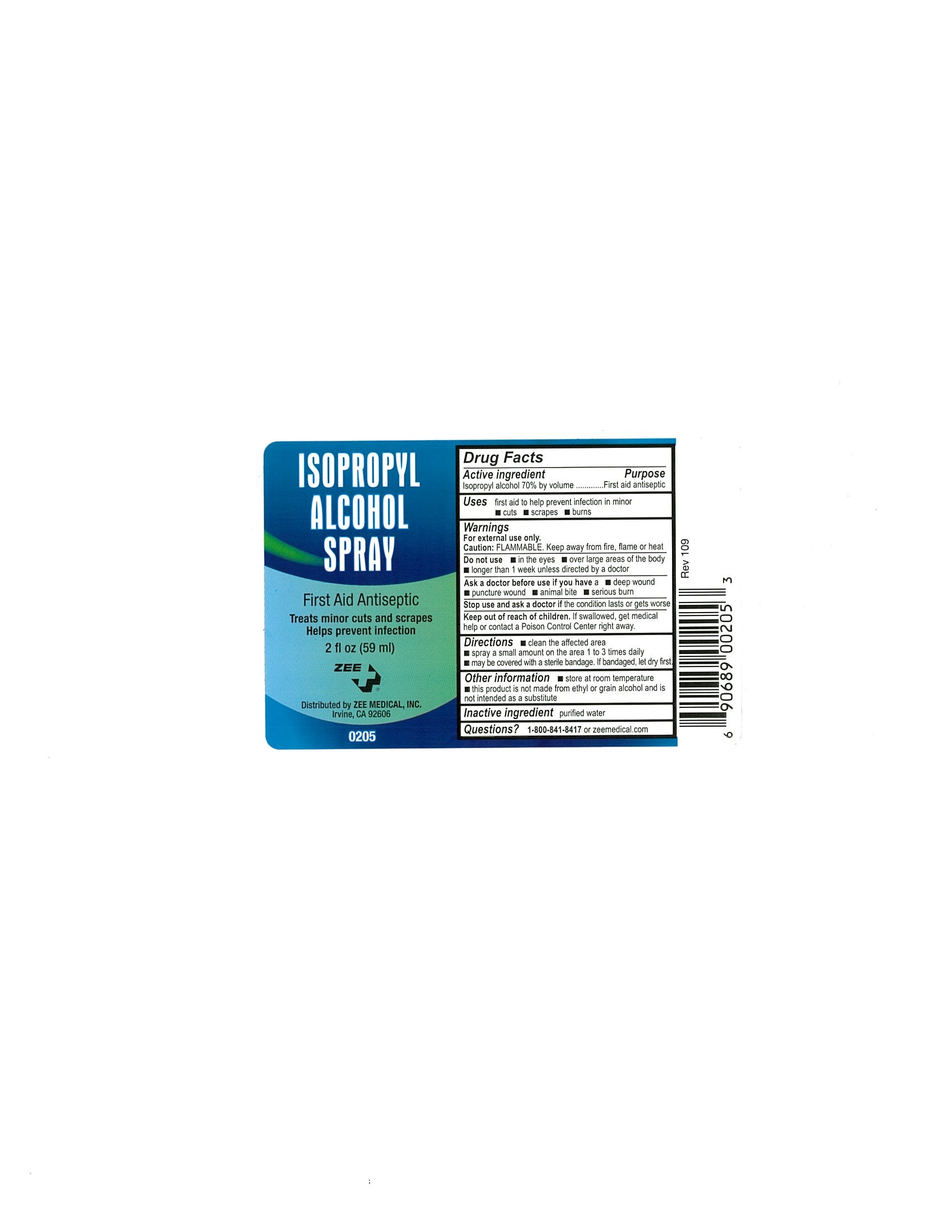 DRUG LABEL: Isopropyl Alcohol
NDC: 42961-049 | Form: SPRAY
Manufacturer: Cintas Corporation
Category: otc | Type: HUMAN OTC DRUG LABEL
Date: 20210107

ACTIVE INGREDIENTS: ALCOHOL 70 mL/100 mL
INACTIVE INGREDIENTS: WATER

Isopropyl Alcohol Spray

Active ingredient

Isopropyl alcohol 70%

Purpose

First aid antiseptic

Uses

first aid to help prevent infection in minor

- cuts
- scrapes
- burns

Warnings

For external use only

Flammable

Caution: FLAMMABLE. Keep away from fire, flame or heat

Do not use

- in the eyes
- over large areas of the body
- longer than 1 week unless directed by a doctor

Ask a doctor before use if you have a

- deep wound
- puncture wound
- animal bite
- serious burns

Stop use and ask a doctor if

- the condition persists or gets worse

Keep out of the reach of children

If swallowed, get medical help or contact a Poison Control Center right away.

Directions

- clean the affected area
- spray a small amount of this product in the area 1 to 3 times daily
- may be covered with a sterile bandage. If bandaged, let dry first

Other information

- store at room temperature
- this product is not made from ethyl or grain alcohol and it is not intended as a substitute

Inactive ingredient

purified water

Questions?

1-800-841-8417 or cintas.com